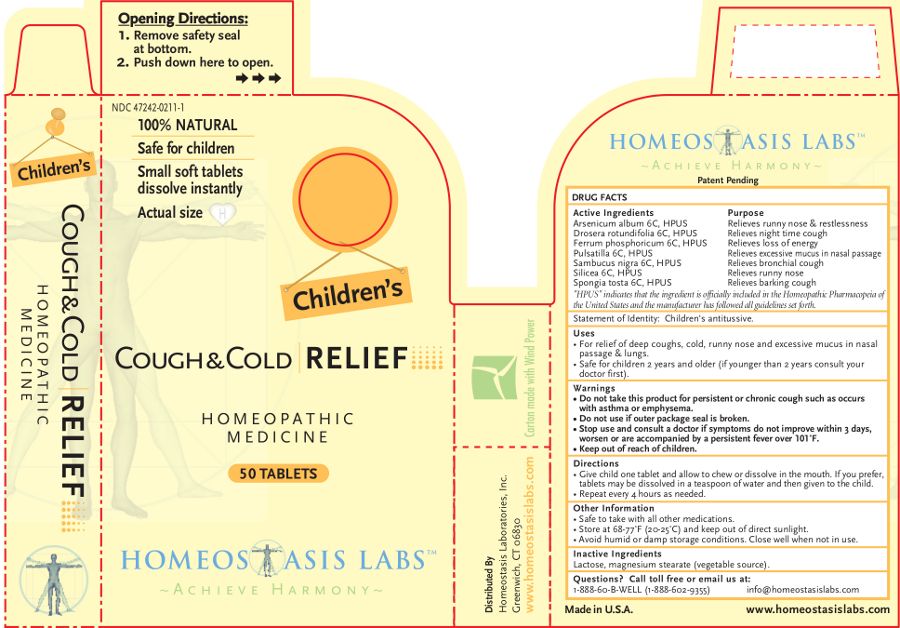 DRUG LABEL: Childrens Cough and Cold RELIEF
NDC: 47242-0211 | Form: TABLET, CHEWABLE
Manufacturer: Homeostasis Laboratories, Inc.
Category: homeopathic | Type: HUMAN OTC DRUG LABEL
Date: 20121114

ACTIVE INGREDIENTS: ARSENIC TRIOXIDE 6 [hp_C]/1 1; FERROSOFERRIC PHOSPHATE 6 [hp_C]/1 1; PULSATILLA VULGARIS 6 [hp_C]/1 1; SILICON DIOXIDE 6 [hp_C]/1 1; DROSERA ROTUNDIFOLIA 6 [hp_C]/1 1; SPONGIA OFFICINALIS SKELETON, ROASTED 6 [hp_C]/1 1; SAMBUCUS NIGRA FLOWERING TOP 6 [hp_C]/1 1
INACTIVE INGREDIENTS: LACTOSE; MAGNESIUM STEARATE

Children's Cough and Cold RELIEF

Active Ingredients | Purpose
Arsenicum album 6C, HPUS | Relieves runny nose & restlessness
Drosera rotundifolia 6C, HPUS | Relieves night timecough
Ferrum phosphoricum 6C, HPUS | Relieves loss of energy
Pulsatilla 6C, HPUS | Relieves excessive mucus in nasal passage
Sambucus nigra 6C, HPUS | Relieves bronchial cough
Silicea 6C, HPUS | Relieves runny nose
Spongia tosta 6C, HPUS | Relieves barking cough

"HPUS" indicates that the ingredient is officially included in the Homeopathic Pharmacopeia of the United States and the manufacturer has followed all guidelines set forth.

Statement of Identity: Children's antitussive.

Uses

For relief of deep coughs, cold, runny nose and excessive mucus in nasal passage & lungs.

Safe for children 2 years and older (if younger than 2 years consult your doctor first).

Warnings

- Do not take this product for persistent or chronic cough such as occurs with asthma or emphysema.
- Do not use if outer package seal is broken.
- Stop use and consult a doctor if symptoms do not improve within 3 days, worsen or are accompanied by a persistent fever over 101˚F.

- Keep out of reach of children.

Directions

Give child one tablet and allow to chew or dissolve in the mouth. If you prefer, tablets may be dissolved in a teaspoon of water and then given to the child.

Repeat every 4 hours as needed.

Other information

- Safe to take with all other medications.
- Store at 68-77°F (20-25°C) and keep out of direct sunlight.
- Avoid humid or damp storage conditions. Close well when not in use.

Inactive Ingredients

Lactose, magnesium stearate (vegetable source).

Questions? Call toll free or email us at:

1-888-60-B-WELL (1-888-602-9355)

info@homeostasislabs.com